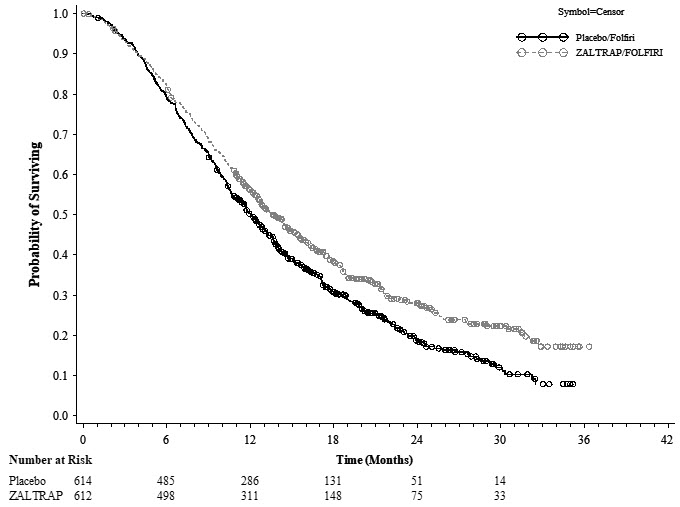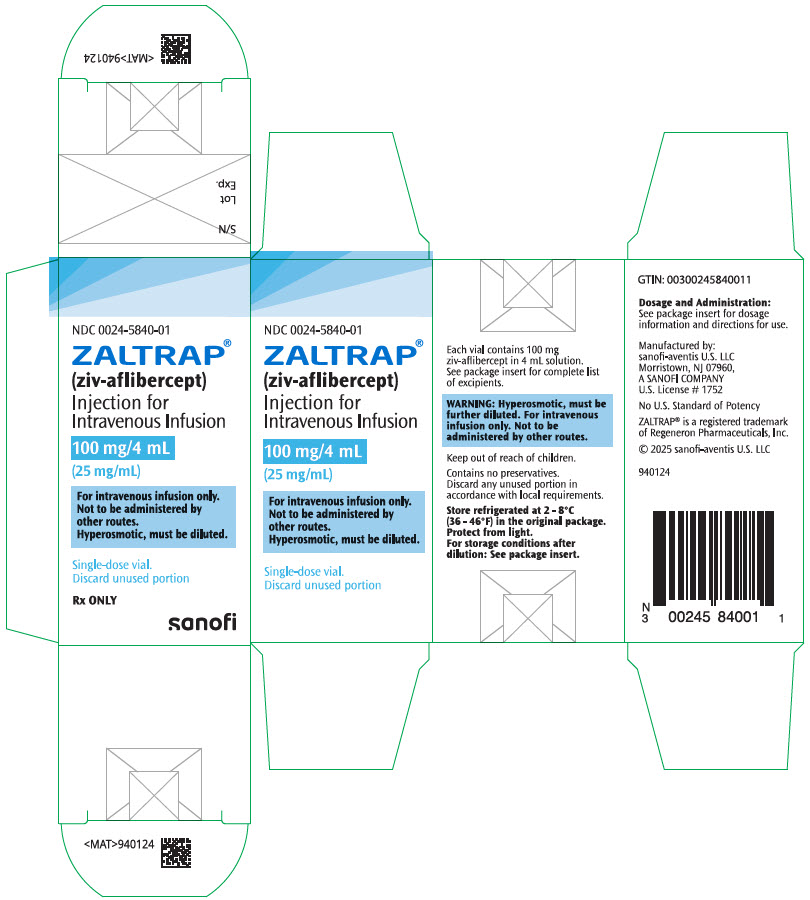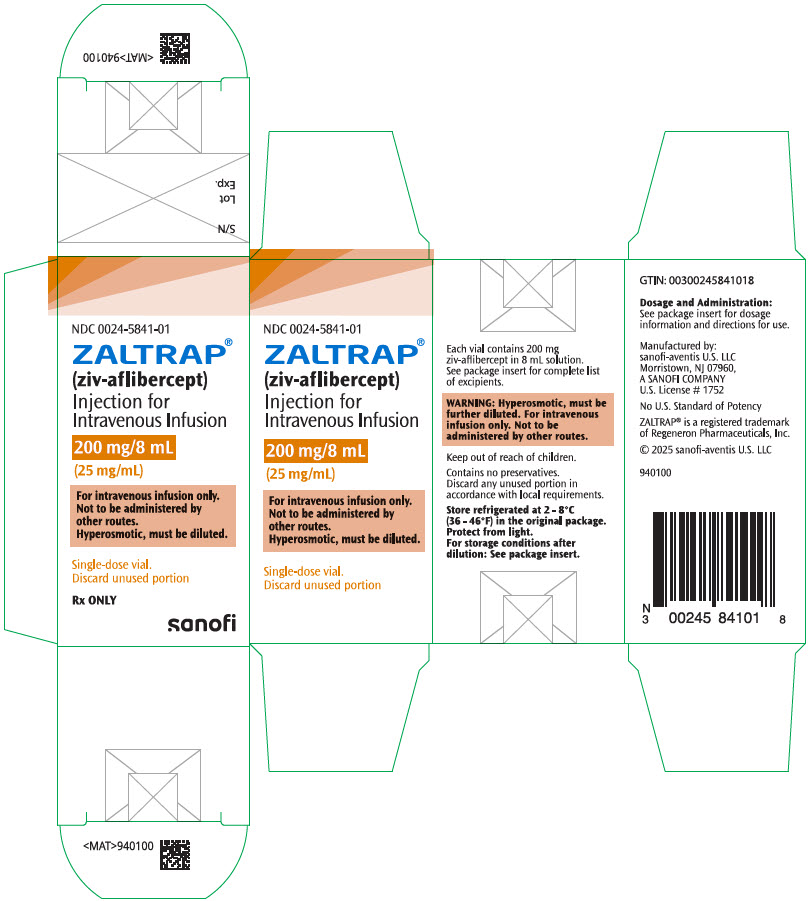 DRUG LABEL: ZALTRAP
NDC: 0024-5840 | Form: SOLUTION, CONCENTRATE
Manufacturer: sanofi-aventis  U.S. LLC
Category: prescription | Type: HUMAN PRESCRIPTION DRUG LABEL
Date: 20251006

ACTIVE INGREDIENTS: AFLIBERCEPT 100 mg/4 mL
INACTIVE INGREDIENTS: SUCROSE; SODIUM CHLORIDE; TRISODIUM CITRATE DIHYDRATE; CITRIC ACID MONOHYDRATE; POLYSORBATE 20; SODIUM PHOSPHATE, DIBASIC, HEPTAHYDRATE; SODIUM PHOSPHATE, MONOBASIC, MONOHYDRATE; SODIUM HYDROXIDE; HYDROCHLORIC ACID; WATER

HIGHLIGHTS OF PRESCRIBING INFORMATION

These highlights do not include all the information needed to use ZALTRAP safely and effectively. See full prescribing information for ZALTRAP.
ZALTRAP® (ziv-aflibercept) injection, for intravenous use
Initial U.S. Approval: 2012

1 INDICATIONS AND USAGE

ZALTRAP, a vascular endothelial growth factor inhibitor, in combination with fluorouracil, leucovorin, irinotecan (FOLFIRI), is indicated for the treatment of patients with metastatic colorectal cancer that is resistant to or has progressed following an oxaliplatin-containing regimen. (1)

2 DOSAGE AND ADMINISTRATION

- 4 mg per kg as an intravenous infusion over 1 hour every 2 weeks. (2.1, 2.3)
- Do not administer as an intravenous push or bolus. (2.3)

3 DOSAGE FORMS AND STRENGTHS

Injection: 100 mg/4 mL (25 mg/mL) and 200 mg/8 mL (25 mg/mL) solution in a single-dose vial (3)

4 CONTRAINDICATIONS

None (4)

5 WARNINGS AND PRECAUTIONS

- Hemorrhage: Severe and sometimes fatal hemorrhage, including gastrointestinal (GI) hemorrhage, has been reported in patients who have received ZALTRAP. Do not administer ZALTRAP to patients with severe hemorrhage. (5.1)
- Gastrointestinal Perforation: Discontinue ZALTRAP therapy in patients who experience GI perforation. (5.2)
- Impaired Wound Healing: Withhold ZALTRAP for at least 4 weeks prior to elective surgery. Do not administer for at least 4 weeks following major surgery and until wounds have adequately healed. Discontinue ZALTRAP in patients with impaired wound healing. The safety of resumption of ZALTRAP after resolution of wound healing complications has not been established. (5.3)
- Fistula Formation: Discontinue ZALTRAP if fistula occurs. (2.2, 5.4)
- Hypertension: Monitor blood pressure and treat hypertension. Temporarily suspend ZALTRAP if hypertension is not controlled. Discontinue ZALTRAP if hypertensive crisis develops. (2.2, 5.5)
- Arterial Thromboembolic Events (ATE): Discontinue ZALTRAP if ATE develops. (5.6)
- Proteinuria: Monitor urine protein. Suspend ZALTRAP for proteinuria of 2 grams per 24 hours or more. Discontinue ZALTRAP if nephrotic syndrome or thrombotic microangiopathy (TMA) develops. (2.2, 5.7)
- Neutropenia and Neutropenic Complications: Delay administration of ZALTRAP/FOLFIRI until neutrophil count is 1.5 × 10^9/L or higher. (5.8)
- Diarrhea and Dehydration: Incidence of severe diarrhea and dehydration is increased. Monitor elderly patients more closely. (5.9, 8.5)
- Reversible Posterior Leukoencephalopathy Syndrome: Discontinue ZALTRAP. (5.10)
- Embryo-Fetal Toxicity: Can cause fetal harm. Advise females of potential risk to fetus and need for use of effective contraception. (5.11, 8.1, 8.3)

6 ADVERSE REACTIONS

Most common adverse reactions (≥20% incidence) were leukopenia, diarrhea, neutropenia, proteinuria, AST increased, stomatitis, fatigue, thrombocytopenia, ALT increased, hypertension, weight decreased, decreased appetite, epistaxis, abdominal pain, dysphonia, serum creatinine increased, and headache. (6.1)

To report SUSPECTED ADVERSE REACTIONS, contact sanofi-aventis at 1-800-633-1610 or FDA at 1-800-FDA-1088 or www.fda.gov/medwatch.

8 USE IN SPECIFIC POPULATIONS

- Lactation: Advise not to breastfeed. (8.2)

FULL PRESCRIBING INFORMATION

1 INDICATIONS AND USAGE

ZALTRAP, in combination with fluorouracil, leucovorin, irinotecan-(FOLFIRI), is indicated for the treatment of patients with metastatic colorectal cancer (mCRC) that is resistant to or has progressed following an oxaliplatin-containing regimen.

2 DOSAGE AND ADMINISTRATION

2.1 Recommended Dose and Schedule

The recommended dosage of ZALTRAP is 4 mg per kg of actual body weight as an intravenous infusion over 1 hour every two weeks in combination with FOLFIRI until disease progression or unacceptable toxicity. Administer ZALTRAP prior to any component of the FOLFIRI regimen on the day of treatment.

Refer to prescribing information for irinotecan, fluorouracil, and leucovorin for the recommended dosage and dosage modifications for these drugs.

2.2 Dosage Modifications for Adverse Reactions

Discontinue ZALTRAP for:

- Severe hemorrhage [see Warnings and Precautions (5.1)]
- Gastrointestinal perforation [see Warnings and Precautions (5.2)]
- Impaired wound healing [see Warnings and Precautions (5.3)]
- Fistula formation [see Warnings and Precautions (5.4)]
- Hypertensive crisis or hypertensive encephalopathy [see Warnings and Precautions (5.5)]
- Arterial thromboembolic events (ATE) [see Warnings and Precautions (5.6)]
- Nephrotic syndrome or thrombotic microangiopathy (TMA) [see Warnings and Precautions (5.7)]
- Reversible posterior leukoencephalopathy syndrome (RPLS) [see Warnings and Precautions (5.10)]

Temporarily suspend ZALTRAP:

- At least 4 weeks prior to elective surgery [see Warnings and Precautions (5.3)].
- For uncontrolled hypertension until controlled. Upon resumption, permanently reduce the ZALTRAP dose to 2 mg per kg [see Warnings and Precautions (5.5)].
- For proteinuria of 2 grams per 24 hours or more. Resume when proteinuria is less than 2 grams per 24 hours. For recurrent proteinuria, suspend ZALTRAP until proteinuria is less than 2 grams per 24 hours and then permanently reduce the ZALTRAP dose to 2 mg per kg [see Warnings and Precautions (5.7)].

2.3 Preparation and Administration

Preparation

Inspect vials visually prior to use. ZALTRAP is a clear, colorless to pale yellow solution. Do not use vial if the solution is discolored or cloudy or if the solution contains particles.

Withdraw the prescribed dose of ZALTRAP and dilute in 0.9% Sodium Chloride Injection, USP or 5% Dextrose Injection, USP to achieve a final concentration of 0.6 mg/mL to 8 mg/mL.

Do not re-enter the vial after the initial puncture. Discard any unused portion left in the vial.

Use polyvinyl chloride (PVC) infusion bags containing bis (2-ethylhexyl) phthalate (DEHP) or polyolefin infusion bags.

Store diluted ZALTRAP refrigerated at 2°C to 8°C (36°F to 46°F) for up to 24 hours or at controlled room temperature of 20°C to 25°C (68°F to 77°F) for up to 8 hours. Discard any unused portion left in the infusion bag.

Administration

Administer the diluted ZALTRAP solution as an intravenous infusion over 1 hour through a 0.2-micron polyethersulfone filter. Do not use filters made of polyvinylidene fluoride (PVDF) or nylon.

Do not administer as an intravenous push or bolus.

Do not combine ZALTRAP with other drugs in the same infusion bag or intravenous line.

Administer ZALTRAP using an infusion set made of one of the following materials:

- PVC containing DEHP
- DEHP free PVC containing trioctyl-trimellitate (TOTM)
- polypropylene
- polyethylene lined PVC
- polyurethane

3 DOSAGE FORMS AND STRENGTHS

ZALTRAP is a clear, colorless to pale-yellow solution available as:

- Injection: 100 mg/4 mL (25 mg/mL) solution in a single-dose vial
- Injection: 200 mg/8 mL (25 mg/mL) solution in a single-dose vial

4 CONTRAINDICATIONS

None.

5 WARNINGS AND PRECAUTIONS

5.1 Hemorrhage

Patients treated with ZALTRAP have an increased risk of hemorrhage, including severe and sometimes fatal hemorrhagic events. In patients with mCRC, bleeding/hemorrhage (all grades) was reported in 38% of patients treated with ZALTRAP/FOLFIRI compared to 19% of patients treated with placebo/FOLFIRI. Grade 3–4 hemorrhagic events, including gastrointestinal hemorrhage, hematuria, and post-procedural hemorrhage, were reported in 3% of patients receiving ZALTRAP/FOLFIRI compared with 1% of patients receiving placebo/FOLFIRI. Severe intracranial hemorrhage and pulmonary hemorrhage/hemoptysis including fatal events have also occurred in patients receiving ZALTRAP.

Monitor patients for signs and symptoms of bleeding. Do not initiate ZALTRAP in patients with severe hemorrhage. Discontinue ZALTRAP in patients who develop severe hemorrhage [see Dosage and Administration (2.2)].

5.2 Gastrointestinal Perforation

Gastrointestinal (GI) perforation including fatal GI perforation can occur in patients receiving ZALTRAP. Across three placebo-controlled clinical studies (colorectal, pancreatic, and lung cancer populations), the incidence of GI perforation (all grades) was 0.8% for patients treated with ZALTRAP and 0.3% for patients treated with placebo. Grade 3–4 GI perforation occurred in 0.8% of patients treated with ZALTRAP and 0.2% of patients treated with placebo.

Monitor patients for signs and symptoms of GI perforation. Discontinue ZALTRAP therapy in patients who experience GI perforation [see Dosage and Administration (2.2)].

5.3 Impaired Wound Healing

Grade 3 impaired wound healing was reported in 2 patients (0.3%) treated with ZALTRAP/FOLFIRI regimen.

Withhold ZALTRAP for at least 4 weeks prior to elective surgery. Do not administer ZALTRAP for at least 4 weeks after major surgery and until wounds have adequately healed. For minor surgery such as central venous access port placement, biopsy, and tooth extraction, ZALTRAP may be initiated/resumed once the surgical wound is fully healed. Discontinue ZALTRAP in patients with impaired wound healing. The safety of resumption of ZALTRAP after resolution of wound healing complications has not been established [see Dosage and Administration (2.2)].

5.4 Fistula Formation

Fistula formation involving gastrointestinal and non-gastrointestinal sites occurs at a higher incidence in patients treated with ZALTRAP. In patients with mCRC, fistulas (anal, enterovesical, enterocutaneous, colovaginal, intestinal sites) were reported in 9 of 611 patients (1.5%) treated with ZALTRAP/FOLFIRI regimen and 3 of 605 patients (0.5%) treated with placebo/FOLFIRI regimen. Grade 3 GI fistula formation occurred in 2 patients treated with ZALTRAP (0.3%) and in 1 patient treated with placebo (0.2%).

Discontinue ZALTRAP therapy in patients who develop fistula [see Dosage and Administration (2.2)].

5.5 Hypertension

ZALTRAP increases the risk of Grade 3–4 hypertension. There is no clinical trial experience administering ZALTRAP to patients with NYHA class III or IV heart failure. In patients with mCRC, Grade 3 hypertension (defined as requiring adjustment in existing antihypertensive therapy or treatment with more than one drug) was reported in 1.5% of patients treated with placebo/FOLFIRI and 19% of patients treated with ZALTRAP/FOLFIRI. Grade 4 hypertension (hypertensive crisis) was reported in 1 patient (0.2%) treated with ZALTRAP/FOLFIRI. Among those patients treated with ZALTRAP/FOLFIRI developing Grade 3–4 hypertension, 54% had onset during the first two cycles of treatment.

Monitor blood pressure every two weeks or more frequently as clinically indicated during treatment with ZALTRAP. Treat with appropriate antihypertensive therapy and continue monitoring blood pressure regularly. Temporarily suspend ZALTRAP in patients with uncontrolled hypertension until controlled and permanently reduce the ZALTRAP dose to 2 mg per kg for subsequent cycles. Discontinue ZALTRAP in patients with hypertensive crisis or hypertensive encephalopathy [see Dosage and Administration (2.2)].

5.6 Arterial Thromboembolic Events

ATE, including transient ischemic attack, cerebrovascular accident, and angina pectoris, occurred more frequently in patients who have received ZALTRAP. In patients with mCRC, ATE was reported in 2.6% of patients treated with ZALTRAP/FOLFIRI and 1.7% of patients treated with placebo/FOLFIRI. Grade 3–4 events occurred in 11 patients (1.8%) treated with ZALTRAP/FOLFIRI and 4 patients (0.7%) treated with placebo/FOLFIRI.

Discontinue ZALTRAP in patients who experience an ATE [see Dosage and Administration (2.2)].

5.7 Proteinuria

Severe proteinuria, nephrotic syndrome, and thrombotic microangiopathy (TMA) occurred more frequently in patients treated with ZALTRAP. In patients with mCRC, proteinuria was reported in 62% patients treated with ZALTRAP/FOLFIRI compared to 41% patients treated with placebo/FOLFIRI. Grade 3–4 proteinuria occurred in 8% of patients treated with ZALTRAP/FOLFIRI compared to 1% of patients treated with placebo/FOLFIRI [see Adverse Reactions (6.1)]. Nephrotic syndrome occurred in 2 patients (0.5%) treated with ZALTRAP/FOLFIRI compared to none of the patients treated with placebo/FOLFIRI. TMA was reported in 3 of 2258 patients with cancer enrolled across completed studies.

Monitor proteinuria by urine dipstick analysis and/or urinary protein creatinine ratio (UPCR) for the development or worsening of proteinuria during ZALTRAP therapy. Patients with a dipstick of ≥2+ for protein or a UPCR greater than 1 should undergo a 24-hour urine collection.

Suspend ZALTRAP administration for proteinuria 2 grams per 24 hours or more, and resume when proteinuria is less than 2 grams per 24 hours. If recurrent, suspend until proteinuria is less than 2 grams per 24 hours and then permanently reduce the ZALTRAP dose to 2 mg per kg. Discontinue ZALTRAP in patients who develop nephrotic syndrome or TMA [see Dosage and Administration (2.2)].

5.8 Neutropenia and Neutropenic Complications

A higher incidence of neutropenic complications (febrile neutropenia and neutropenic infection) occurred in patients receiving ZALTRAP. In patients with mCRC, Grade 3–4 neutropenia occurred in 37% of patients treated with ZALTRAP/FOLFIRI compared to 30% patients treated with placebo/FOLFIRI [see Adverse Reactions (6.1)]. Grade 3–4 febrile neutropenia occurred in 4% of patients treated with ZALTRAP/FOLFIRI compared to 2% of patients treated with placebo/FOLFIRI. Grade 3–4 neutropenic infection/sepsis occurred in 1.5% of patients treated with ZALTRAP/FOLFIRI and 1.2% of patients treated with placebo/FOLFIRI.

Monitor CBC with differential count at baseline and prior to initiation of each cycle of ZALTRAP. Delay ZALTRAP/FOLFIRI until neutrophil count is at or above 1.5 × 10^9/L.

5.9 Diarrhea and Dehydration

The incidence of severe diarrhea is increased in patients treated with ZALTRAP/FOLFIRI. In patients with mCRC, Grade 3–4 diarrhea was reported in 19% of patients treated with ZALTRAP/FOLFIRI compared to 8% of patients treated with placebo/FOLFIRI. Grade 3–4 dehydration was reported in 4% of patients treated with ZALTRAP/FOLFIRI compared to 1% of patients treated with placebo/FOLFIRI [see Adverse Reactions (6.1)]. The incidence of diarrhea is increased in patients who are age 65 years or older as compared to patients younger than 65 years of age [see Use in Specific Populations (8.5)]. Monitor elderly patients closely for diarrhea.

5.10 Reversible Posterior Leukoencephalopathy Syndrome

RPLS (also known as posterior reversible encephalopathy syndrome) was reported in 0.5% of 3795 patients treated with ZALTRAP monotherapy or in combination with chemotherapy.

Confirm the diagnosis of RPLS with magnetic resonance imaging (MRI) and discontinue ZALTRAP in patients who develop RPLS. Symptoms usually resolve or improve within days, although some patients have experienced ongoing neurologic sequelae or death [see Dosage and Administration (2.2)].

5.11 Embryo-Fetal Toxicity

Based on findings from animal studies and its mechanism of action, ZALTRAP can cause fetal harm when administered to pregnant women. Administration of ziv-aflibercept during the period of organogenesis was embryotoxic and teratogenic in rabbits at exposure levels approximately 0.3 times the human exposure at the 4 mg per kg dose. Advise pregnant women of the potential risk to a fetus. Advise females of reproductive potential to use effective contraception during treatment with ZALTRAP and for 3 months following the last dose [see Use in Specific Populations (8.1, 8.3)].

6 ADVERSE REACTIONS

The following clinically significant adverse reactions are described elsewhere in the labeling:

- Hemorrhage [see Warnings and Precautions (5.1)]
- Gastrointestinal Perforation [see Warnings and Precautions (5.2)]
- Impaired Wound Healing [see Warnings and Precautions (5.3)]
- Fistula Formation [see Warnings and Precautions (5.4)]
- Hypertension [see Warnings and Precautions (5.5)]
- Arterial Thromboembolic Events [see Warnings and Precautions (5.6)]
- Proteinuria [see Warnings and Precautions (5.7)]
- Neutropenia and Neutropenic Complications [see Warnings and Precautions (5.8)]
- Diarrhea and Dehydration [see Warnings and Precautions (5.9)]
- Reversible Posterior Leukoencephalopathy Syndrome [see Warnings and Precautions (5.10)]

6.1 Clinical Trials Experience

Because clinical trials are conducted under widely varying conditions, adverse reaction rates observed in the clinical trials of a drug cannot be directly compared to rates in the clinical trials of another drug and may not reflect the rates observed in practice.

The safety of ZALTRAP in combination with FOLFIRI was evaluated in VELOUR (EFC102621) [see Clinical Studies (14)]. Patients received ZALTRAP 4 mg per kg (N=611) or placebo (N=605) intravenously every two weeks (one cycle) in combination with FOLFIRI. Patients received a median of 9 cycles of ZALTRAP/FOLFIRI.

The most common Grade 3–4 adverse reactions (≥5%) in the ZALTRAP/FOLFIRI arm were neutropenia, diarrhea, hypertension, leukopenia, stomatitis, fatigue, proteinuria, and asthenia.

The most frequent adverse reactions leading to permanent discontinuation in ≥1% of patients treated with ZALTRAP/FOLFIRI regimen were asthenia/fatigue, infections, diarrhea, dehydration, hypertension, stomatitis, venous thromboembolic events, neutropenia, and proteinuria.

The ZALTRAP dose was reduced and/or omitted in 17% of patients. Cycle delays >7 days occurred in 60% of patients treated with ZALTRAP/FOLFIRI.

The most common adverse reactions (≥20%) in the ZALTRAP/FOLFIRI arm were leukopenia, diarrhea, neutropenia, proteinuria, AST increased, stomatitis, fatigue, thrombocytopenia, ALT increased, hypertension, weight decreased, decreased appetite, epistaxis, abdominal pain, dysphonia, serum creatinine increased, and headache.

Adverse reactions and laboratory abnormalities that occurred in ≥5% (all grades) of patients receiving ZALTRAP in combination with FOLFIRI and which occurred at ≥2% higher frequency in patients who received ZALTRAP/FOLFIRI compared to those who received placebo/FOLFIRI in VELOUR are shown in Table 1. VELOUR was not designed to demonstrate a statistically significant difference in adverse reaction rates for ZALTRAP/FOLFIRI as compared to placebo/FOLFIRI for any adverse reactions listed below.

Table 1: Selected Adverse Reactions and Laboratory Findings in VELOUR
Primary System Organ Class Preferred Term | ZALTRAP/ FOLFIRI (N=611) |  | Placebo/ FOLFIRI (N=605)
Primary System Organ Class Preferred Term | All grades (%) | Grades 3–4 (%) | All grades (%) | Grades 3–4 (%)
Blood and lymphatic system disorders
Leukopenia | 78 | 16 | 72 | 12
Neutropenia | 67 | 37 | 57 | 30
Thrombocytopenia | 48 | 3 | 35 | 2
Gastrointestinal disorders
Diarrhea | 69 | 19 | 57 | 8
Stomatitis | 50 | 13 | 33 | 5
Abdominal Pain | 27 | 4 | 24 | 2
Abdominal Pain Upper | 11 | 1 | 8 | 1
Hemorrhoids | 6 | 0 | 2 | 0
Rectal Hemorrhage | 5 | 0.7 | 2 | 0.5
Proctalgia | 5 | 0.3 | 2 | 0.3
Investigations
AST increased | 62 | 3 | 54 | 2
ALT increased | 50 | 3 | 39 | 2
Weight decreased | 32 | 3 | 14 | 0.8
Renal and urinary disorders
Proteinuria [Compilation of clinical and laboratory data] | 62 | 8 | 41 | 1
Serum creatinine increased | 23 | 0 | 19 | 0.5
General disorders and administration site conditions
Fatigue | 48 | 13 | 39 | 8
Asthenia | 18 | 5 | 13 | 3
Vascular disorders
Hypertension | 41 | 19 | 11 | 1.5
Metabolism and nutrition disorders
Decreased Appetite | 32 | 3 | 24 | 2
Dehydration | 9 | 4 | 3 | 1
Respiratory, thoracic and mediastinal disorders
Epistaxis | 28 | 0.2 | 7 | 0
Dysphonia | 25 | 0.5 | 3 | 0
Dyspnea | 12 | 0.8 | 9 | 0.8
Oropharyngeal Pain | 8 | 0.2 | 3 | 0
Rhinorrhea | 6 | 0 | 2 | 0
Nervous system disorders
Headache | 22 | 2 | 9 | 0.3
Skin and subcutaneous tissue disorders
Palmar-Plantar Erythrodysesthesia Syndrome | 11 | 3 | 4 | 0.5
Skin Hyperpigmentation | 8 | 0 | 3 | 0
Infections
Urinary Tract Infection | 9 | 0.8 | 6 | 0.8
Note: Adverse Reactions are reported using MedDRA version 13.1 and graded using NCI CTC version 3.0

Infections occurred at a higher frequency in patients receiving ZALTRAP/FOLFIRI (46%, all grades; 12%, Grade 3–4) than in patients receiving placebo/FOLFIRI (33%, all grades; 7%, Grade 3–4), including urinary tract infection, nasopharyngitis, upper respiratory tract infection, pneumonia, catheter site infection, and tooth infection.

In patients with mCRC, severe hypersensitivity reactions have been reported with ZALTRAP/FOLFIRI (0.3%) and placebo/FOLFIRI (0.5%).

In patients with mCRC, venous thromboembolic events (VTE), consisting primarily of deep venous thrombosis and pulmonary embolism, occurred in 9% of patients treated with ZALTRAP/FOLFIRI and 7% of patients treated with placebo/FOLFIRI. Grade 3–4 VTE occurred in 8% of patients treated with ZALTRAP/FOLFIRI and in 6% of patients treated with placebo/FOLFIRI. Pulmonary embolism occurred in 5% of patients treated with ZALTRAP/FOLFIRI and 3.4% of patients treated with placebo/FOLFIRI.

6.2 Immunogenicity

As with all therapeutic proteins, there is a potential for immunogenicity. The detection of antibody formation is highly dependent on the sensitivity and specificity of the assay. Additionally, the observed incidence of antibody (including neutralizing antibody) positivity in an assay may be influenced by several factors including assay methodology, sample handling, timing of sample collection, concomitant medications, and underlying disease. For these reasons, comparison of the incidence of antibodies in the studies described below with the incidence of antibodies in other studies or to other products may be misleading.

In patients with various cancers across 15 studies, 1.4% (41/2862) of patients tested positive for antiproduct antibody (APA) at baseline. The incidence of APA development was 3.1% (53/1687) in patients receiving intravenous ziv-aflibercept and 1.7% (19/1134) in patients receiving placebo. Among patients who tested positive for APA and had sufficient samples for further testing, neutralizing antibodies were detected in 17 of 48 ziv-aflibercept-treated patients and in 2 of 40 patients receiving placebo.

The mean free ziv-aflibercept trough concentrations were lower in patients with positive neutralizing antibodies than in the overall population. The impact of neutralizing antibodies on efficacy and safety could not be assessed based on limited available data.

6.3 Postmarketing Experience

The following adverse reactions have been identified during postapproval use of ZALTRAP. Because these reactions are reported voluntarily from a population of uncertain size, it is not always possible to reliably estimate their frequency or establish a causal relationship to drug exposure.

Musculoskeletal and connective tissue disorders: Osteonecrosis of the jaw

Cardiac disorders: Cardiac failure, ejection fraction decreased

Vascular disorders: Arterial (including aortic) aneurysms, dissections, and rupture

7 DRUG INTERACTIONS

No dedicated drug-drug interaction studies have been conducted for ZALTRAP. No clinically important pharmacokinetic interactions were found between ziv-aflibercept and irinotecan/SN-38 or fluorouracil [see Clinical Pharmacology (12.3)].

8 USE IN SPECIFIC POPULATIONS

8.1 Pregnancy

Risk Summary

Based on findings from animal reproduction studies and its mechanism of action [see Clinical Pharmacology (12.1)], ZALTRAP can cause fetal harm when administered to pregnant women. There is insufficient data in pregnant women exposed to ZALTRAP to assess the risks. Administration of ziv-aflibercept during the period of organogenesis was embryotoxic and teratogenic in rabbits at exposure levels approximately 0.3 times the human exposure at the 4 mg per kg dose (see Data). Advise pregnant women of the potential risk to a fetus.

In the U.S. general population, the estimated background risk of major birth defects and miscarriage in clinically recognized pregnancies is 2% to 4% and 15% to 20%, respectively.

Data

Animal data

In pregnant rabbits, administration of ziv-aflibercept during the period of organogenesis resulted in an increase in postimplantation loss and external (including anasarca, umbilical hernia, diaphragmatic hernia and gastroschisis, cleft palate, ectrodactyly, and anal atresia), visceral (heart, great vessels, and arteries), and skeletal fetal malformations (including fused vertebrae, sternebrae, and ribs, supernumerary arches and ribs, and incomplete ossification) at doses greater than or equal to 3 mg per kg, administered once every 3 days (approximately 0.3 times the human exposure at the 4 mg per kg dose based on AUC).

8.2 Lactation

Risk Summary

There are no data on the presence of ziv-aflibercept in human milk, or the effects of ziv-aflibercept on the breastfed infant or on milk production. Because of the potential for serious adverse reactions in breastfed infants, advise women not to breastfeed during treatment with ZALTRAP and for 1 month following the last dose.

8.3 Females and Males of Reproductive Potential

ZALTRAP can cause fetal harm when administered to a pregnant woman [see Use in Specific Populations (8.1)].

Pregnancy Testing

Verify the pregnancy status in females of reproductive potential prior to initiating ZALTRAP [see Use in Specific Populations (8.1)].

Contraception

Females

Based on data from animal studies and its mechanism of action, ZALTRAP can cause fetal harm when administered to pregnant women [see Use in Specific Populations (8.1)].

Advise female patients of reproductive potential to use effective contraception during treatment with ZALTRAP and for 3 months following the last dose.

Infertility

Advise female and male patients of reproductive potential that ZALTRAP may impair reproductive function and fertility [see Nonclinical Toxicology (13.1)].

8.4 Pediatric Use

The safety and effectiveness in pediatric patients have not been established. Safety and efficacy were assessed, but not established in a dose-escalation, safety, and tolerability study (NCT00622414) in 21 patients with solid tumors 2 to 21 years of age (median age 12.9). The mean elimination half-life of free ziv-aflibercept determined after the first dose in 8 pediatric patients aged 5 to 17 years was within the range of values previously observed in adults. The maximum tolerated dose based on body weight in these pediatric patients was lower than the dose known to be safe and effective in adults with mCRC.

Juvenile Animal Toxicity Data

Weekly/every-two-weeks intravenous administration of ziv-aflibercept at dose of 3 mg per kg (approximately 0.6 times the human exposure at the 4 mg per kg dose based on AUC) to growing young adult (sexually mature) cynomolgus monkeys for up to 6 months resulted in changes in the bone (effects on growth plate and the axial and appendicular skeleton), nasal cavity (atrophy/loss of the septum and/or turbinates), kidney (glomerulopathy with inflammation), ovary (decreased number of maturing follicles, granulosa cells, and/or theca cells), and adrenal gland (decreased vacuolation with inflammation). In another study in sexually immature cynomolgus monkeys (treated intravenously for 3 months), there were similar effects. The skeletal and nasal cavity effects were not reversible after a post-dosing recovery period.

8.5 Geriatric Use

Of the 611 patients with mCRC, patients treated with ZALTRAP/FOLFIRI, 205 (34%) were 65 years or older, and 33 (5%) were 75 years or older. Elderly patients (≥65 years of age) experienced higher incidences (≥5%) of diarrhea, dizziness, asthenia, weight decrease, and dehydration when compared to younger patients. Monitor elderly patients more closely for diarrhea and dehydration [see Warnings and Precautions (5.9)].

The effect of ZALTRAP on overall survival was similar in patients <65 years old and ≥65 years old who received ZALTRAP/FOLFIRI.

8.6 Renal Impairment

No dosage modification is recommended for patients with renal impairment [see Clinical Pharmacology (12.3)].

8.7 Hepatic Impairment

No dosage modification is recommended for patients with mild (total bilirubin >1 to 1.5 times upper limit normal [ULN] and any aspartate transaminase [AST]) and moderate (total bilirubin >1.5 to 3 times ULN and any AST) hepatic impairment [see Clinical Pharmacology (12.3)]. ZALTRAP has not been studied in patients with severe hepatic impairment (total bilirubin >3 times ULN and any AST).

11 DESCRIPTION

Ziv-aflibercept is a vascular endothelial growth factor inhibitor. It is a recombinant fusion protein consisting of Vascular Endothelial Growth Factor (VEGF)-binding portions from the extracellular domains of human VEGF Receptors 1 and 2 fused to the Fc portion of the human IgG1. Ziv-aflibercept is produced by recombinant DNA technology in a Chinese hamster ovary (CHO) K-1 mammalian expression system. Ziv-aflibercept is a dimeric glycoprotein with a protein molecular weight of 97 kilodaltons (kDa) and contains glycosylation, constituting an additional 15% of the total molecular mass, resulting in a total molecular weight of 115 kDa.

ZALTRAP (ziv-aflibercept) injection is a sterile, clear, colorless to pale-yellow, non-pyrogenic, preservative-free, solution for intravenous use. ZALTRAP is supplied in single-dose vials of 100 mg/4 mL and 200 mg/8 mL formulated as 25 mg/mL ziv-aflibercept in polysorbate 20 (1 mg/mL), sodium chloride (5.84 mg/mL), sodium citrate (1.45 mg/mL), sodium phosphate (0.8 mg/mL), and sucrose (200 mg/mL), in Water for Injection, USP, at a pH of 6.2.

12 CLINICAL PHARMACOLOGY

12.1 Mechanism of Action

Ziv-aflibercept acts as a soluble receptor that binds to human VEGF-A (equilibrium dissociation constant KD of 0.5 pM for VEGF-A165 and 0.36 pM for VEGF-A121), to human VEGF-B (KD of 1.92 pM), and to human PlGF (KD of 39 pM for PlGF-2). By binding to these endogenous ligands, ziv-aflibercept can inhibit the binding and activation of their cognate receptors. This inhibition can result in decreased neovascularization and decreased vascular permeability.

In animals, ziv-aflibercept was shown to inhibit the proliferation of endothelial cells, thereby inhibiting the growth of new blood vessels. Ziv-aflibercept inhibited the growth of xenotransplanted colon tumors in mice.

12.2 Pharmacodynamics

Cardiac Electrophysiology

The effect of 6 mg per kg intravenous ZALTRAP every three weeks on QTc interval was evaluated in 87 patients with solid tumors in a randomized, placebo-controlled study. No large changes in the mean QT interval from baseline (i.e., greater than 20 ms as corrected for placebo) based on Fridericia correction method were detected in the study. However, a small increase in the mean QTc interval (i.e., less than 10 ms) cannot be excluded due to limitations of the study design.

12.3 Pharmacokinetics

Plasma concentrations of free and VEGF-bound ziv-aflibercept were measured using specific enzyme-linked immunosorbent assays (ELISA). Free ziv-aflibercept concentrations appear to exhibit linear pharmacokinetics in the dose range of 2 mg per kg to 9 mg per kg. Steady state concentrations of free ziv-aflibercept were reached by the second dose. The accumulation ratio for free ziv-aflibercept was approximately 1.2 after administration of 4 mg per kg every two weeks.

Elimination

Following a dose of 4 mg per kg every two weeks administered intravenously, the elimination half-life of free ziv-aflibercept was approximately 6 days (range 4–7 days).

Specific Populations

Based on a population pharmacokinetic analysis, age, race, and sex did not have a clinically important effect on the exposure of free ziv-aflibercept. Patients weighing ≥100 kg had a 29% increase in systemic exposure compared to patients weighing 50 to 100 kg.

Patients with hepatic impairment

Based on a population pharmacokinetic analysis which included patients with mild (total bilirubin >1 to 1.5 times ULN and any AST, n=63) and moderate (total bilirubin >1.5 to 3 times ULN and any AST, n=5) hepatic impairment, there was no effect of total bilirubin, AST, and alanine aminotransferase on the clearance of free ziv-aflibercept. There are no data available for patients with severe hepatic impairment (total bilirubin >3 times ULN and any AST).

Patients with renal impairment

Based on a population pharmacokinetic analysis which included patients with mild (CLCR 50–80 mL/min, n=549), moderate (CLCR 30–50 mL/min, n=96), and severe renal impairment (CLCR <30 mL/min, n=5), there was no clinically important effect of creatinine clearance on the clearance of free ziv-aflibercept.

Drug Interaction Studies

No clinically meaningful interaction was found between ziv-aflibercept and irinotecan or fluorouracil based on cross-study comparisons and population pharmacokinetic analyses.

13 NONCLINICAL TOXICOLOGY

13.1 Carcinogenesis, Mutagenesis, Impairment of Fertility

No studies have been conducted to evaluate carcinogenicity or mutagenicity of ziv-aflibercept.

Ziv-aflibercept impaired reproductive function and fertility in monkeys. In a 6-month repeat-dose toxicology study in sexually mature monkeys, ziv-aflibercept inhibited ovarian function and follicular development, as evidenced by: decreased ovary weight, decreased amount of luteal tissue, decreased number of maturing follicles, atrophy of uterine endometrium and myometrium, vaginal atrophy, abrogation of progesterone peaks and menstrual bleeding. Alterations in sperm morphology and decreased sperm motility were present in male monkeys. These effects were observed at all doses tested including the lowest dose tested, 3 mg per kg. Reversibility was observed within 18 weeks after cessation of treatment. Systemic exposure (AUC) with a 3 mg per kg per dose in monkeys was approximately 0.6 times the AUC in patients at the 4 mg per kg dose.

13.2 Animal Toxicology and/or Pharmacology

Repeated administration of ziv-aflibercept resulted in a delay in wound healing in rabbits. In full-thickness excisional and incisional skin wound models, ziv-aflibercept administration reduced fibrous response, neovascularization, epidermal hyperplasia/re-epithelialization, and tensile strength.

14 CLINICAL STUDIES

The efficacy of ZALTRAP was evaluated in VELOUR (NCT00561470), a randomized (1:1), double-blind, placebo-controlled study in patients with mCRC who are resistant to or have progressed during or within 6 months of receiving oxaliplatin-based combination chemotherapy, with or without prior bevacizumab. Patients were randomized to receive either ZALTRAP 4 mg per kg intravenously over 1 hour on day 1 or placebo in combination with FOLFIRI (irinotecan 180 mg/m^2 intravenously over 90 minutes and leucovorin [dl racemic] 400 mg/m^2 intravenously over 2 hours at the same time on day 1 using a Y-line, followed by fluorouracil 400 mg/m^2 as an intravenous bolus and then by fluorouracil 2400 mg/m^2 as a continuous intravenous infusion over 46 hours). The treatment cycles on both arms were repeated every 2 weeks. Patients were treated until disease progression or unacceptable toxicity. Randomization was stratified by the Eastern Cooperative Oncology Group performance status (PS) (0 versus 1 versus 2) and according to prior therapy with bevacizumab (yes or no). The major efficacy outcome measure was overall survival (OS). Additional efficacy outcome measures were progression-free survival (PFS) and overall response rate (ORR).

Demographics characteristics were similar between treatment arms. A total of 1226 patients were randomized, 612 to the ZALTRAP arm and 614 to the placebo arm. The median age was 61 years, 59% were men, 87% were White, 7% were Asian, 3.5% were Black, and 98% had a baseline ECOG PS of 0 or 1. Among the 1226 randomized patients, 89% and 90% of patients treated with placebo/FOLFIRI and ZALTRAP/FOLFIRI, respectively, received prior oxaliplatin-based combination chemotherapy in the metastatic/advanced setting. A total of 346 patients (28%) received bevacizumab in combination with the prior oxaliplatin-based treatment.

Efficacy results are summarized in Figure 1 and Table 2.

Figure 1: Kaplan-Meier Curves of Overall Survival for VELOUR

Table 2: Main Efficacy Outcome Measures for VELOUR [PFS (based on tumor assessment by the IRC): Significance threshold is set to 0.0001.]
 | ZALTRAP/FOLFIRI N=612 | Placebo/FOLFIRI N=614
Overall Survival
Number of deaths, n (%) | 403 (65.8%) | 460 (74.9%)
Median overall survival (95% CI) (months) | 13.50 (12.52, 14.95) | 12.06 (11.07, 13.08)
Stratified Hazard ratio (95% CI) | 0.817 (0.714, 0.935)
Stratified Log-Rank test p-value | 0.0032
Progression Free Survival (PFS)
Number of events, n (%) | 393 (64.2%) | 454 (73.9%)
Median PFS (95% CI) (months) | 6.90 (6.51, 7.20) | 4.67 (4.21, 5.36)
Stratified Hazard ratio (95% CI) | 0.758 (0.661, 0.869)
Stratified Log-Rank test p-value [Stratified on ECOG Performance Status (0 vs 1 vs 2) and Prior Bevacizumab (yes vs no)] | 0.00007
Overall Response Rate (ORR)
ORR (CR+PR) (95% CI) [Overall objective response rate by IRC] | 19.8% (16.4%, 23.2%) | 11.1% (8.5%, 13.8%)
Stratified Cochran-Mantel-Haenszel test p-value | 0.0001

Planned subgroup analyses for overall survival based on stratification factors at randomization yielded an HR of 0.86 (95% CI: 0.68, 1.1) in patients who received prior bevacizumab and an HR of 0.79 (95% CI: 0.67, 0.93) in patients without prior bevacizumab exposure.

16 HOW SUPPLIED/STORAGE AND HANDLING

ZALTRAP (ziv-aflibercept) injection is a clear, colorless to pale-yellow solution supplied in single-dose vials with a concentration of 25 mg/mL.

NDC 0024-5840-01: carton containing one single-dose vial of 100 mg/4 mL (25 mg/mL)

NDC 0024-5841-01: carton containing one single-dose vial of 200 mg/8 mL (25 mg/mL)

STORAGE AND HANDLING

Store ZALTRAP vials in a refrigerator at 2°C to 8°C (36°F to 46°F). Keep the vials in the original outer carton to protect from light. Discard unused portion.

17 PATIENT COUNSELING INFORMATION

Hemorrhage

- Inform patients that ZALTRAP can cause severe bleeding and advise patients to contact their healthcare provider for bleeding or symptoms of bleeding, including lightheadedness [see Warnings and Precautions (5.1)].

Gastrointestinal Perforation and Fistula Formation

- Advise patients to immediately contact their healthcare provider for signs and symptoms of gastrointestinal perforation or fistula [see Warnings and Precautions (5.2, 5.4)].

Impaired Wound Healing

- Advise patients that ZALTRAP may impair wound healing. Instruct patients to discuss any planned surgical procedure (including tooth extractions) with all their healthcare providers [see Warnings and Precautions (5.3)].

Hypertension

- Inform patients that ZALTRAP can cause or exacerbate existing hypertension. Advise patients to undergo routine blood pressure monitoring and to contact their healthcare provider if blood pressure is elevated or if symptoms from hypertension occur including severe headache, lightheadedness, or neurologic symptoms [see Warnings and Precautions (5.5)].

Arterial Thromboembolic Events

- Inform patients of an increased risk of ATE [see Warnings and Precautions (5.6)].

Proteinuria

- Advise patients that they will need to undergo regular laboratory tests to monitor protein in their urine [see Warnings and Precautions (5.7)].

Neutropenia and Neutropenic Complications

- Advise patients to notify their healthcare provider of fever or other signs of infection [see Warnings and Precautions (5.8)].

Diarrhea and Dehydration

- Advise patients to notify their healthcare provider of severe diarrhea, vomiting, or severe abdominal pain [see Warnings and Precautions (5.9)].

Posterior Reversible Leukoencephalopathy Syndrome

- Advise patients to immediately contact their healthcare provider for new onset or worsening neurological function [see Warnings and Precautions (5.10)].

Embryo-Fetal Toxicity

Advise females of reproductive potential:

- of the potential risk to a fetus. Advise females to inform their healthcare provider of a known or suspected pregnancy [see Warnings and Precautions (5.11), Use in Specific Populations (8.1)].
- to use effective contraception during treatment with ZALTRAP and for 3 months following the last dose [see Use in Specific Populations (8.3)].

Lactation

- Advise women not to breastfeed during treatment with ZALTRAP and for 1 month following the last dose [see Use in Specific Populations (8.2)].

Aneurysms and Artery Dissections

- Advise patients to notify their healthcare provider if they have or have had an aneurysm (swelling/enlargement and weakening of part of a blood vessel) or artery dissection (tear in a blood vessel wall) [see Adverse Reactions (6.3)].

Manufactured by:
sanofi-aventis U.S. LLC
Morristown, NJ 07960
A SANOFI COMPANY
U.S. License No. 1752

ZALTRAP is a registered trademark of Regeneron Pharmaceuticals, Inc.

©2025 sanofi-aventis U.S. LLC

PRINCIPAL DISPLAY PANEL - 100 mg/4 mL Vial Carton

NDC 0024-5840-01

ZALTRAP®
(ziv-aflibercept)
Injection for
Intravenous Infusion

100 mg/4 mL
(25 mg/mL)

For intravenous infusion only.
Not to be administered by
other routes.
Hyperosmotic, must be diluted.

Single-dose vial.
Discard unused portion

Rx ONLY

sanofi

PRINCIPAL DISPLAY PANEL - 200 mg/8 mL Vial Carton

NDC 0024-5841-01

ZALTRAP®
(ziv-aflibercept)
Injection for
Intravenous Infusion

200 mg/8 mL
(25 mg/mL)

For intravenous infusion only.
Not to be administered by
other routes.
Hyperosmotic, must be diluted.

Single-dose vial.
Discard unused portion

Rx ONLY

sanofi